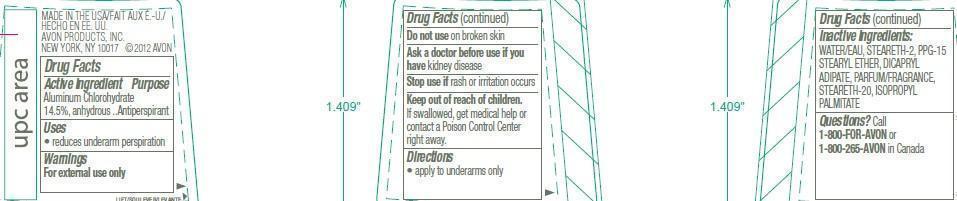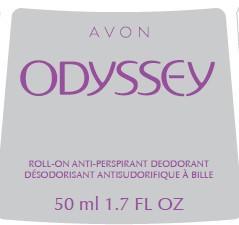 DRUG LABEL: Odyssey
NDC: 10096-9360 | Form: GEL
Manufacturer: New Avon LLC
Category: otc | Type: HUMAN OTC DRUG LABEL
Date: 20190322

ACTIVE INGREDIENTS: ALUMINUM CHLOROHYDRATE 145 mg/1 mL
INACTIVE INGREDIENTS: WATER

Odyssey Anti-Perspirant Roll-On Deodorant

Active ingredient

Aluminum Chlorohydrate 14.5%, anhydrous..

Purpose

..Antiperspirant

Uses

•reduces underarm perspiration

Warnings

For external use only

Do not use on broken skin

Ask a doctor before use if you have kidney disease

Stop use if rash or irritation occurs

Keep out of reach of children. If swallowed, get medical help or contact a poison control center right away.

Directions

•apply to underarms only

Inactive ingredients

WATER/EAU, STEARETH-2, PPG-15 STEARYL ETHER, DICAPRYL ADIPATE, PARFUM/FRAGRANCE, STEARETH-20, ISOPROPYL PALMITATE

Questions?

Call 1-800-FOR-AVON or 1 -800-265-AVON in Canada